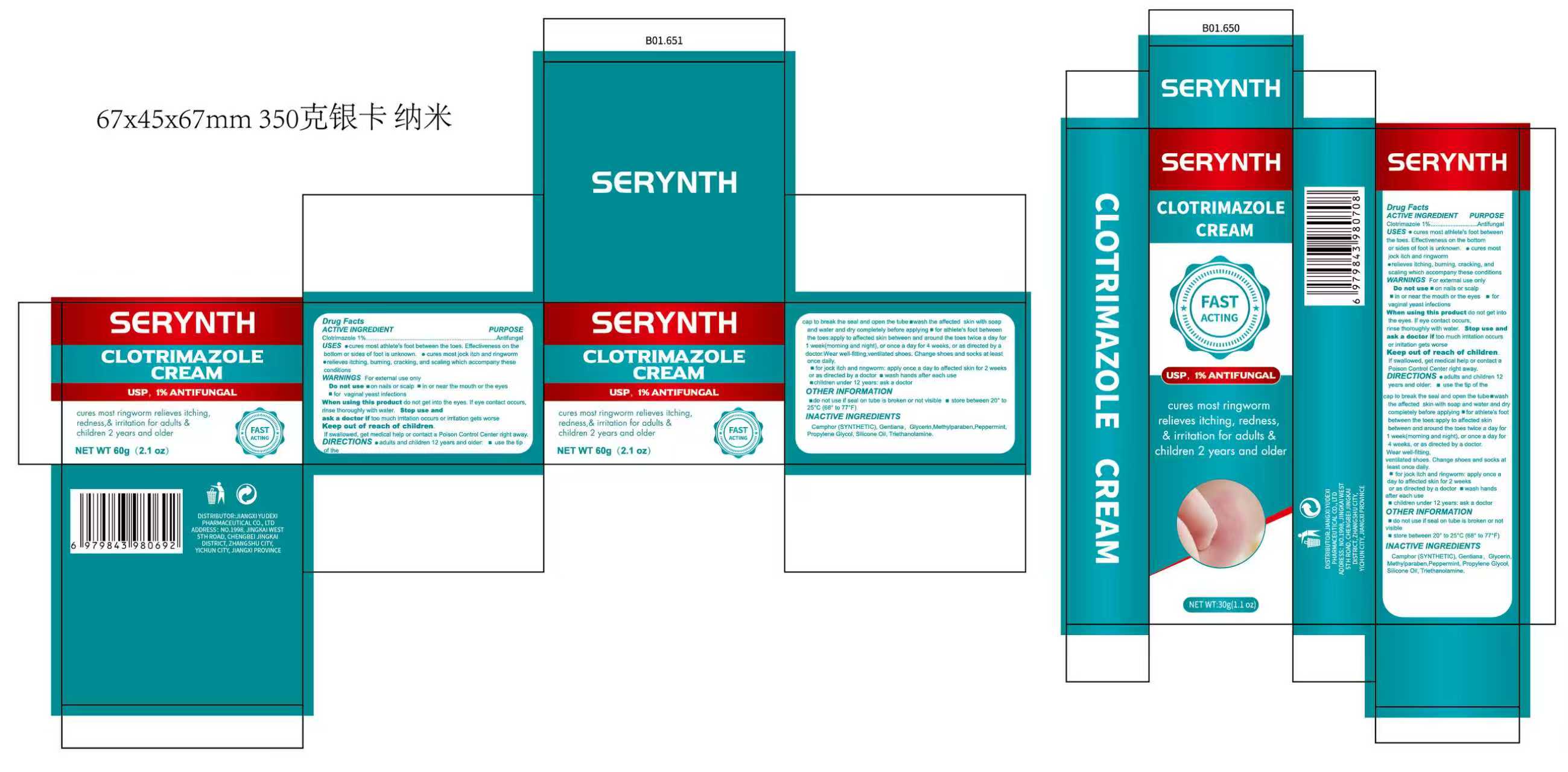 DRUG LABEL: SERYNTH  Clotrimazole
NDC: 85248-101 | Form: CREAM
Manufacturer: Jiangxi Yudexi Pharmaceutical Co., LTD
Category: otc | Type: HUMAN OTC DRUG LABEL
Date: 20260208

ACTIVE INGREDIENTS: CLOTRIMAZOLE 1 g/100 g
INACTIVE INGREDIENTS: GENTIANA MANSHURICA ROOT; GLYCERIN; PEPPERMINT; CAMPHOR (SYNTHETIC); METHYLPARABEN; DIMETHICONE; TRIETHANOLAMINE; PROPYLENE GLYCOL

85248-101

Active Ingredient

Clotrimazole 1%

Purpose

Antifungal

Use

·cures most athlete's foot between the toes. Effectiveness on the bottom or sides of foot is unknown. ·cures most jock itch and ringworm ·relieves itching.burning, cracking, and scaling which accompany these conditions

Warnings

For external use only

Do not use

■on nails or scalp ■in or near the mouth or the eyes ■for vaginal yeast infections

When Using

do not get into the eyes. lf eye contact occurs, rinse thoroughly with water.

Stop Use

too much irritation occurs or irritation gets worse

Ask Doctor

for jock itch and ringworm: apply once a day to affected skin for 2 weeks or as directed by a doctor wash hands after each use children under 12 years: ask a doctor

Keep Oot Of Reach Of Children

If swallowed, get medical help or contact a Poison Control Center right away.

Directions

·adults and children 12 years and older■ use the tip of the cap to break the seal and open the tube ■wash the affected skin with soap and water and dry completely before applying■ for athlete's foot between the toes:apply to affected skin between and around the toes twice a day for 1 week(morning and night), or once a day for 4 weeks, or as directed by a doctor. Wear well-fitting, ventilated shoes. Change shoes and socks at least once daily.
■for jock itch and ringworm: apply once a day to affected skin for 2 weeks or as directed by a doctor ■wash hands after each use ■children under 12 years: ask a doctor

Other information

■do not use if seal on tube is broken or not visible■ store between 20° to 25℃(68° to 77°F)

Inactive ingredients

Camphor (SYNTHETIC).Gentiana.Glycerin.Methylparaben,Peppermint, Propylene Glycol, Silicone Oil, Triethanolamine